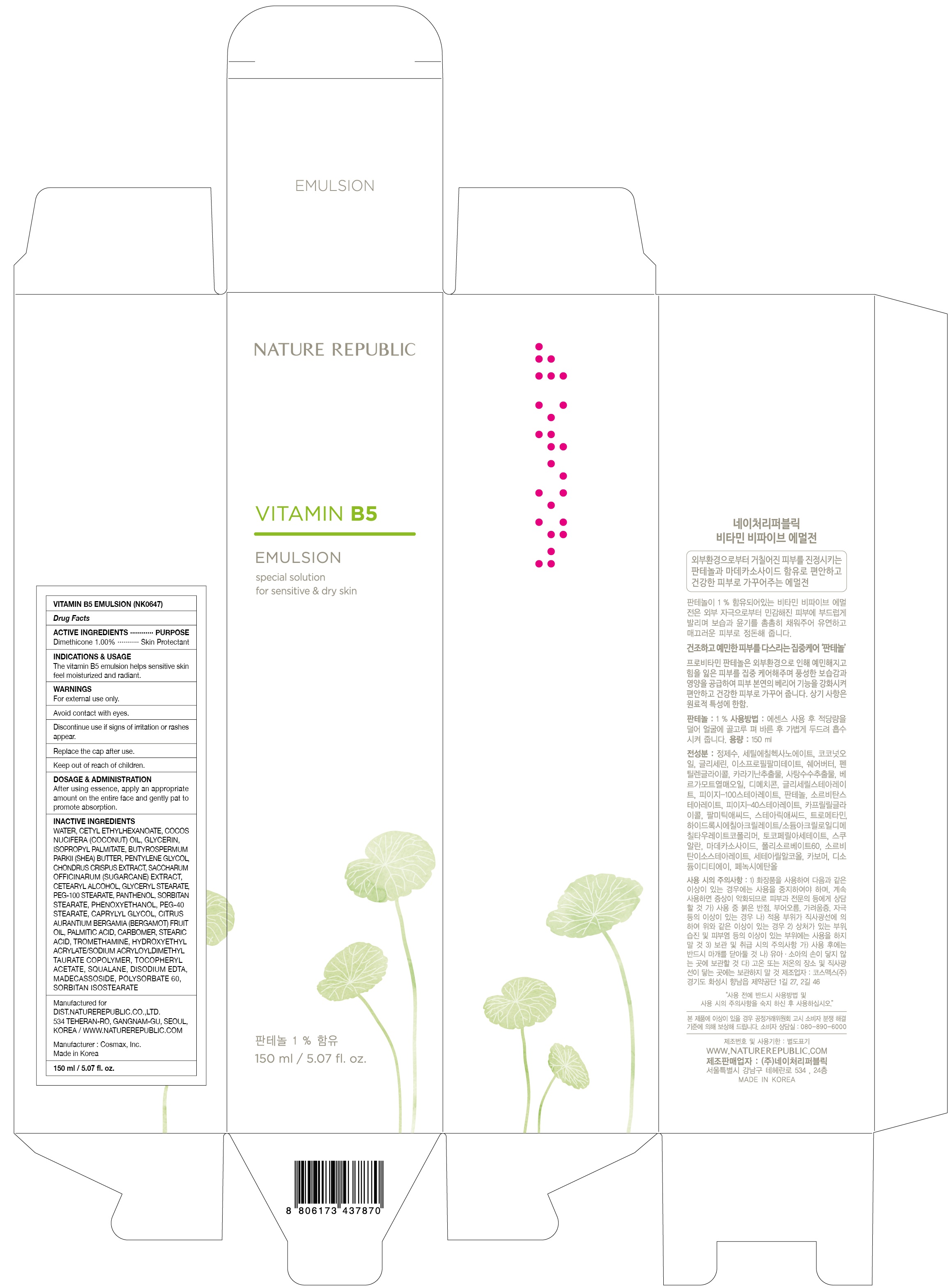 DRUG LABEL: VITAMIN B5
NDC: 51346-435 | Form: EMULSION
Manufacturer: NATURE REPUBLIC CO., LTD.
Category: otc | Type: HUMAN OTC DRUG LABEL
Date: 20170119

ACTIVE INGREDIENTS: Dimethicone 1.50 g/150 mL
INACTIVE INGREDIENTS: Water; Cetyl Ethylhexanoate

ACTIVE INGREDIENT

Active ingredients: Dimethicone 1.00%

INACTIVE INGREDIENT

Inactive ingredients: Water, Cetyl Ethylhexanoate, Cocos Nucifera (Coconut) Oil, Glycerin, Isopropyl Palmitate, Butyrospermum Parkii (Shea) Butter, Pentylene Glycol, Chondrus Crispus Extract, Saccharum Officinarum (Sugarcane) Extract, Cetearyl Alcohol, Glyceryl Stearate, PEG-100 Stearate, Panthenol, Sorbitan Stearate, Phenoxyethanol, PEG-40 Stearate, Caprylyl Glycol, Citrus Aurantium Bergamia (Bergamot) Fruit Oil, Palmitic Acid, Carbomer, Stearic Acid, Tromethamine, Hydroxyethyl Acrylate/Sodium Acryloyldimethyl Taurate Copolymer, Tocopheryl Acetate, Squalane, Disodium EDTA, Madecassoside, Polysorbate 60, Sorbitan Isostearate

PURPOSE

Purpose: Skin Protectant

WARNINGS

Warnings: For external use only. Avoid contact with eyes and mouth. Discontinue use if signs of irritation or rashes appear. Keep out of reach of children. Replace the cap after use.

KEEP OUT OF REACH OF CHILDREN

INDICATIONS & USAGE

Indications & Usage: The vitamin B5 emulsion helps sensitive skin feel moisturized and radiant.

DOSAGE & ADMINISTRATION

Dosage & Administration: After using essence, apply an appropriate amount on the entire face and gently pat to promote absorption.